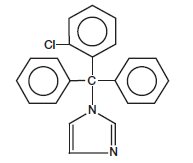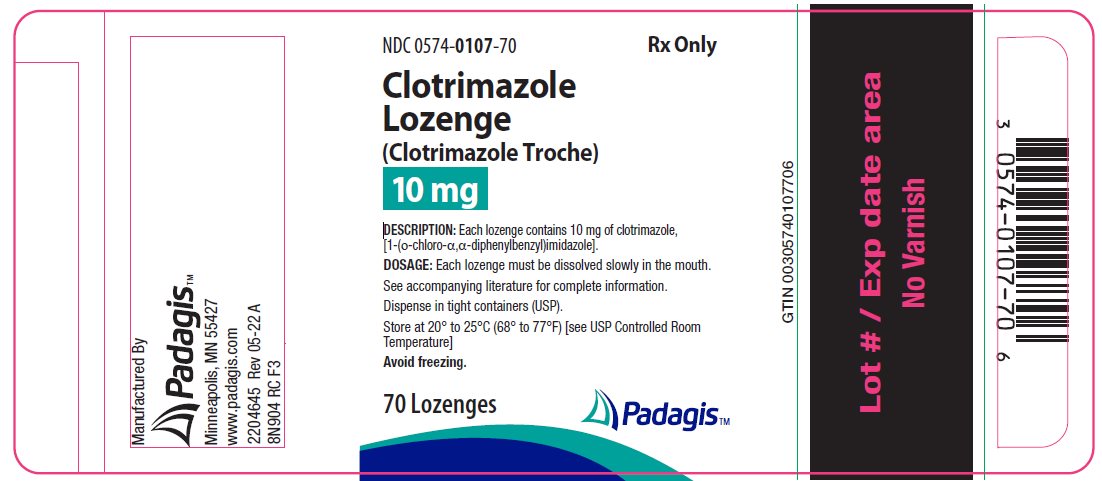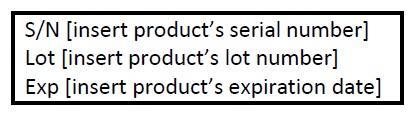 DRUG LABEL: Clotrimazole
NDC: 0574-0107 | Form: LOZENGE
Manufacturer: Padagis US LLC
Category: prescription | Type: HUMAN PRESCRIPTION DRUG LABEL
Date: 20220531

ACTIVE INGREDIENTS: CLOTRIMAZOLE 10 mg/1 1
INACTIVE INGREDIENTS: DEXTROSE, UNSPECIFIED FORM; MICROCRYSTALLINE CELLULOSE; POVIDONE, UNSPECIFIED; MAGNESIUM STEARATE

Clotrimazole Lozenge
(Clotrimazole Troche)

FOR TOPICAL ORAL ADMINISTRATION

DESCRIPTION

Each clotrimazole lozenge contains 10 mg clotrimazole [1-(o-chloro-α, α-diphenylbenzyl) imidazole], a synthetic antifungal agent, for topical use in the mouth.

Structural Formula:

Chemical Formula:

C22H17ClN2

The lozenge dosage form is a large, slowly dissolving tablet (troche) containing 10 mg of clotrimazole dispersed in dextrose, microcrystalline cellulose, povidone, and magnesium stearate.

CLINICAL PHARMACOLOGY

Clotrimazole is a broad-spectrum antifungal agent that inhibits the growth of pathogenic yeasts by altering the permeability of cell membranes. The action of clotrimazole is fungistatic at concentrations of drug up to 20 mcg/mL and may be fungicidal in vitro against Candida albicans and other species of the genus Candida at higher concentrations. No single-step or multiple-step resistance to clotrimazole has developed during successive passages of Candida albicans in the laboratory; however, individual organism tolerance has been observed during successive passages in the laboratory. Such in vitro tolerance has resolved once the organism has been removed from the antifungal environment.

After oral administration of a 10 mg clotrimazole lozenge to healthy volunteers, concentrations sufficient to inhibit most species of Candida persist in saliva for up to three hours following the approximately 30 minutes needed for a lozenge to dissolve. The long term persistence of drug in saliva appears to be related to the slow release of clotrimazole from the oral mucosa to which the drug is apparently bound. Repetitive dosing at three hour intervals maintains salivary levels above the minimum inhibitory concentrations of most strains of Candida; however, the relationship between in vitro susceptibility of pathogenic fungi to clotrimazole and prophylaxis or cure of infections in humans has not been established.

In another study, the mean serum concentrations were 4.98 ± 3.7 and 3.23 ± 1.4 nanograms/mL of clotrimazole at 30 and 60 minutes, respectively, after administration as a lozenge.

INDICATIONS AND USAGE

Clotrimazole lozenges are indicated for the local treatment of oropharyngeal candidiasis. The diagnoses should be confirmed by a KOH smear and/or culture prior to treatment.

Clotrimazole lozenges are also indicated prophylactically to reduce the incidence of oropharyngeal candidiasis in patients immunocompromised by conditions that include chemotherapy, radiotherapy, or steroid therapy utilized in the treatment of leukemia, solid tumors, or renal transplantation. There are no data from adequate and well-controlled trials to establish the safety and efficacy of this product for prophylactic use in patients immunocompromised by etiologies other than those listed in the previous sentence. (See DOSAGE AND ADMINISTRATION.)

CONTRAINDICATIONS

Clotrimazole lozenges are contraindicated in patients who are hypersensitive to any of its components.

WARNING

Clotrimazole lozenges are not indicated for the treatment of systemic mycoses including systemic candidiasis.

PRECAUTIONS

Abnormal liver function tests have been reported in patients treated with clotrimazole lozenges; elevated SGOT levels were reported in about 15% of patients in the clinical trials. In most cases the elevations were minimal and it was often impossible to distinguish effects of clotrimazole from those of other therapy and the underlying disease (malignancy in most cases). Periodic assessment of hepatic function is advisable particularly in patients with pre-existing hepatic impairment.

Since patients must be instructed to allow each lozenge to dissolve slowly in the mouth in order to achieve maximum effect of the medication, they must be of such an age and physical and/or mental condition to comprehend such instructions.

Carcinogenesis:

An 18 month dosing study with clotrimazole in rats has not revealed any carcinogenic effect.

Usage in Pregnancy:

Pregnancy Category C:

Clotrimazole has been shown to be embryotoxic in rats and mice when given in doses 100 times the adult human dose (in mg/kg), possibly secondary to maternal toxicity. The drug was not teratogenic in mice, rabbits, and rats when given in doses up to 200, 180, and 100 times the human dose.

Clotrimazole given orally to mice from nine weeks before mating through weaning at a dose 120 times the human dose was associated with impairment of mating, decreased number of viable young, and decreased survival to weaning. No effects were observed at 60 times the human dose. When the drug was given to rats during a similar time period at 50 times the human dose, there was a slight decrease in the number of pups per litter and decreased pup viability.

There are no adequate and well controlled studies in pregnant women. Clotrimazole lozenges should be used during pregnancy only if the potential benefit justifies the potential risk to the fetus.

PEDIATRIC USE

Safety and effectiveness of clotrimazole in children below the age of 3 years have not been established; therefore, its use in such patients is not recommended.

The safety and efficacy of the prophylactic use of clotrimazole lozenges in children have not been established.

GERIATRIC USE

Clinical studies of clotrimazole did not include sufficient numbers of subjects aged 65 and over to determine whether they respond differently from younger subjects. Other reported clinical experience has not identified differences in responses between the elderly and younger patients.

ADVERSE REACTIONS

Abnormal liver function tests have been reported in patients treated with clotrimazole lozenges; elevated SGOT levels were reported in about 15% of patients in the clinical trials (See Precautions section).

Nausea, vomiting, unpleasant mouth sensations and pruritus have also been reported with the use of the lozenge.

OVERDOSAGE

No data available.

DRUG ABUSE AND DEPENDENCE

No data available.

DOSAGE AND ADMINISTRATION

Clotrimazole lozenges must be slowly dissolved in the mouth. The recommended dose is one lozenge five times a day for fourteen consecutive days. Only limited data are available on the safety and effectiveness of the clotrimazole lozenge after prolonged administration; therefore, therapy should be limited to short term use, if possible.

For prophylaxis to reduce the incidence of oropharyngeal candidiasis in patients immunocompromised by conditions that include chemotherapy, radiotherapy, or steroid therapy utilized in the treatment of leukemia, solid tumors, or renal transplantation, the recommended dose is one lozenge three times daily for the duration of chemotherapy or until steroids are reduced to maintenance levels.

HOW SUPPLIED

Clotrimazole lozenges, 10 mg, white discoid, uncoated tablets, debossed with "PAD" over "0107" on one side and plain on the other, are supplied as follows:

 | Strength | NDC Code | Lozenge Identification
Bottles of 70: | 10 mg | 0574-0107-70 | PAD 0107
Bottles of 140: | 10 mg | 0574-0107-14 | PAD 0107
Boxes of 70 foil packs: | 10 mg | 0574-0107-77 | PAD 0107

STORAGE AND HANDLING

Store at 20° to 25°C (68° to 77°F) [see USP Controlled Room Temperature]

Avoid freezing.

Rx Only

Manufactured By Padagis
Minneapolis, MN 55427
2204645 Rev 05-22A

8N904 RC F3

PRINCIPAL DISPLAY PANEL

NDC 0574-0107-70

Rx Only

Clotrimazole Lozenge (Clotrimazole Troche) 10 mg

DESCRIPTION: Each lozenge contains 10 mg of clotrimazole, [1-(ο-chloro-α,α-diphenylbenzyl)imidazole].

DOSAGE: Each lozenge must be dissolved slowly in the mouth.

See accompanying literature for complete information.

Dispense in tight containers (USP).

Store at 20° to 25°C (68° to 77°F) [see USP Controlled Room Temperature]

Avoid freezing.

70 Lozenges

The following image is a placeholder representing the product identifier that is either affixed or imprinted on the drug package label during the packaging operation.